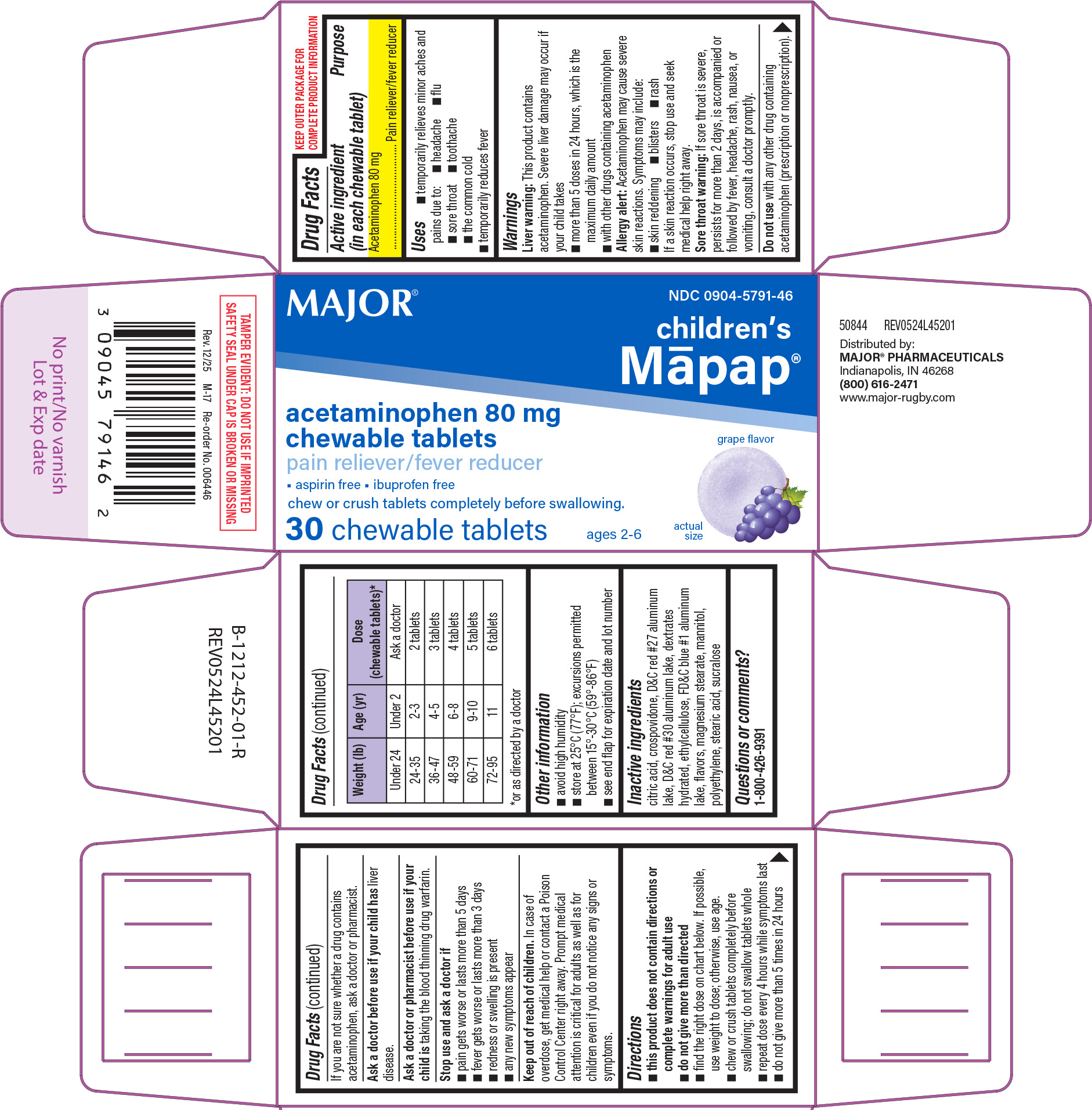 DRUG LABEL: Childrens Mapap
NDC: 0904-5791 | Form: TABLET, CHEWABLE
Manufacturer: Major Pharmaceuticals
Category: otc | Type: HUMAN OTC DRUG LABEL
Date: 20260204

ACTIVE INGREDIENTS: ACETAMINOPHEN 80 mg/1 1
INACTIVE INGREDIENTS: CITRIC ACID MONOHYDRATE; CROSPOVIDONE, UNSPECIFIED; D&C RED NO. 27 ALUMINUM LAKE; D&C RED NO. 30 ALUMINUM LAKE; DEXTROSE MONOHYDRATE; ETHYLCELLULOSE, UNSPECIFIED; FD&C BLUE NO. 1 ALUMINUM LAKE; MAGNESIUM STEARATE; MANNITOL; HIGH DENSITY POLYETHYLENE; STEARIC ACID; SUCRALOSE

Major 44-452

Active ingredient (in each chewable tablet)

Acetaminophen 80 mg

Purpose

Pain reliever/fever reducer

Uses

- temporarily relieves minor aches and pains due to:
  - headache
  - toothache
  - sore throat
  - the common cold
  - flu
- temporarily reduces fever

Warnings

Liver warning: This product contains acetaminophen. Severe liver damage may occur if your child takes

- more than 5 doses in 24 hours, which is the maximum daily amount
- with other drugs containing acetaminophen

Allergy alert: Acetaminophen may cause severe skin reactions. Symptoms may include:

- skin reddening
- blisters
- rash

If a skin reaction occurs, stop use and seek medical help right away.

Sore throat warning: If sore throat is severe, persists for more than 2 days, is accompanied or followed by fever, headache, rash, nausea, or vomiting, consult a doctor promptly.

Do not use

with any other drug containing acetaminophen (prescription or nonprescription). If you are not sure whether a drug contains acetaminophen, ask a doctor or pharmacist.

Ask a doctor before use if your child has

liver disease.

Ask a doctor or pharmacist before use if your child is

taking the blood thinning drug warfarin.

Stop use and ask a doctor if

- pain gets worse or lasts more than 5 days
- fever gets worse or lasts more than 3 days
- redness or swelling is present
- any new symptoms appear

Keep out of reach of children.

In case of overdose, get medical help or contact a Poison Control Center right away. Prompt medical attention is critical for adults as well as for children even if you do not notice any signs or symptoms.

Directions

- this product does not contain directions or complete warnings for adult use
- do not give more than directed
- find the right dose on chart below. If possible, use weight to dose; otherwise, use age.
- chew or crush tablets completely before swallowing; do not swallow tablets whole
- repeat dose every 4 hours while symptoms last
- do not give more than 5 times in 24 hours

Weight (lb) | Age (yr) | Dose (chewable tablets)*
Under 24 | Under 2 | Ask a doctor
24-35 | 2-3 | 2 tablets
36-47 | 4-5 | 3 tablets
48-59 | 6-8 | 4 tablets
60-71 | 9-10 | 5 tablets
72-95 | 11 | 6 tablets

*or as directed by a doctor

Other information

- avoid high humidity
- store at 25ºC (77ºF); excursions permitted between 15°-30°C (59°-86°F)
- see end flap for expiration date and lot number

Inactive ingredients

citric acid, crospovidone, D&C red #27 aluminum lake, D&C red #30 aluminum lake, dextrates hydrated, ethylcellulose, FD&C blue #1 aluminum lake, flavors, magnesium stearate, mannitol, polyethylene, stearic acid, sucralose

Questions or comments?

1-800-426-9391

Principal Display Panel

MAJOR®

NDC 0904-5791-46

Children's
Māpap®

ACETAMINOPHEN
80 mg Chewable Tablets

Pain reliever / Fever reducer

ASPIRIN FREE • IBUPROFEN FREE

AGES 2-6

30 Chewable Tablets

Actual Size

Chew or crush tablets completely before swallowing.

Grape Flavor

TAMPER EVIDENT: DO NOT USE IF IMPRINTED
SAFETY SEAL UNDER CAP IS BROKEN OR MISSING

50844 REV0524L45201

Distributed by:
MAJOR® PHARMACEUTICALS
Indianapolis, IN 46268
(800) 616-2471
www.major-rugby.com
Rev. 12/25 M-17 Re-order No. 006446

Major 44-452